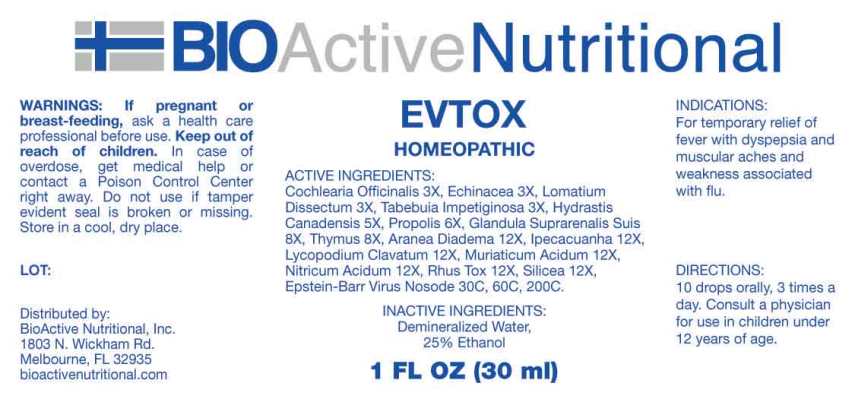 DRUG LABEL: EVTOX
NDC: 43857-0531 | Form: LIQUID
Manufacturer: BioActive Nutritional, Inc.
Category: homeopathic | Type: HUMAN OTC DRUG LABEL
Date: 20240419

ACTIVE INGREDIENTS: COCHLEARIA OFFICINALIS FLOWERING TOP 3 [hp_X]/1 mL; ECHINACEA ANGUSTIFOLIA WHOLE 3 [hp_X]/1 mL; LOMATIUM DISSECTUM ROOT 3 [hp_X]/1 mL; TABEBUIA IMPETIGINOSA BARK 3 [hp_X]/1 mL; GOLDENSEAL 5 [hp_X]/1 mL; PROPOLIS WAX 6 [hp_X]/1 mL; SUS SCROFA ADRENAL GLAND 8 [hp_X]/1 mL; SUS SCROFA THYMUS 8 [hp_X]/1 mL; ARANEUS DIADEMATUS 12 [hp_X]/1 mL; IPECAC 12 [hp_X]/1 mL; LYCOPODIUM CLAVATUM SPORE 12 [hp_X]/1 mL; HYDROCHLORIC ACID 12 [hp_X]/1 mL; NITRIC ACID 12 [hp_X]/1 mL; TOXICODENDRON PUBESCENS LEAF 12 [hp_X]/1 mL; SILICON DIOXIDE 12 [hp_X]/1 mL; HUMAN HERPESVIRUS 4 30 [hp_C]/1 mL
INACTIVE INGREDIENTS: WATER; ALCOHOL

DRUG FACTS:

ACTIVE INGREDIENTS:

Cochlearia Officinalis 3X, Echinacea (Angustifolia) 3X, Lomatium Dissectum 3X, Tabebuia Impetiginosa 3X, Hydrastis Canadensis 5X, Propolis 6X, Glandula Suprarenalis Suis 8X, Thymus (Suis) 8X, Aranea Diadema 12X, Ipecacuanha 12X, Lycopodium Clavatum 12X, Muriaticum Acidum 12X, Nitricum Acidum 12X, Rhus Tox 12X, Silicea 12X, Epstein-Barr Virus Nosodes 30C, 60C, 200C.

INDICATIONS:

For temporary relief of fever with dyspepsia and muscular aches and weakness associated with flu.

WARNINGS:

If pregnant or breast-feeding, ask a health care professional before use.

Keep out of reach of children. In case of overdose, get medical help or contact a Poison Control Center right away.

Do not use if tamper evident seal is broken or missing.

Store in a cool, dry place.

KEEP OUT OF REACH OF CHILDREN:

In case of overdose, get medical help or contact a Poison Control Center right away.

DIRECTIONS:

10 drops orally, 3 times a day. Consult a physician for use in children under 12 years of age.

INDICATIONS:

For temporary relief of fever with dyspepsia and muscular aches and weakness associated with flu.

INACTIVE INGREDIENTS:

Demineralized Water, 25% Ethanol

QUESTIONS:

BioActive Nutritional, Inc.

1803 N. Wickham Rd.

Melbourne, FL 32935

bioactivenutritional.com

*For a complete list of EBV Nosodes contact BioActive Nutritional, Inc.

PACKAGE LABEL DISPLAY:

BIOActive Nutritional

EVTOX

HOMEOPATHIC

1 FL OZ (30 ml)